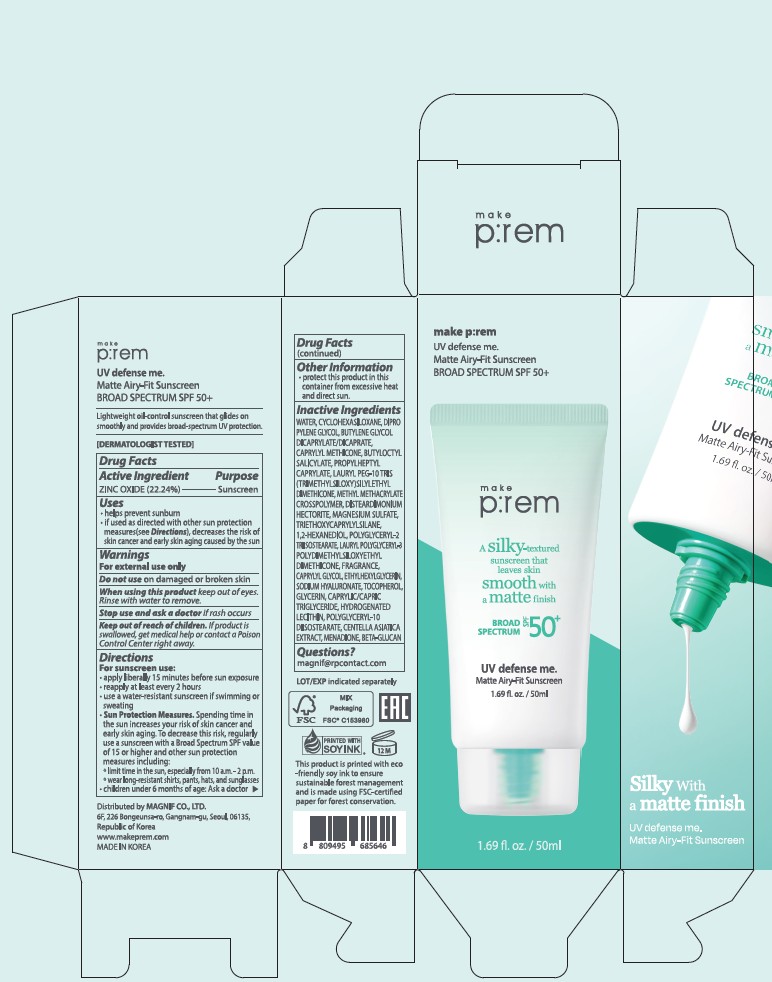 DRUG LABEL: UV Defense me. Matte Airy-Fit Sunscreen
NDC: 84523-102 | Form: CREAM
Manufacturer: MAGNIF CO., LTD
Category: otc | Type: HUMAN OTC DRUG LABEL
Date: 20251210

ACTIVE INGREDIENTS: ZINC OXIDE 11.12 g/50 mL
INACTIVE INGREDIENTS: CAPRYLIC/CAPRIC TRIGLYCERIDE; MENADIONE; BUTYLENE GLYCOL DICAPRYLATE/DICAPRATE; WATER; POLYGLYCERYL-2 TRIISOSTEARATE; GLYCERIN; CENTELLA ASIATICA TRITERPENOIDS; PROPYLHEPTYL CAPRYLATE; SODIUM HYALURONATE; CAPRYLYL METHICONE; 1,2-HEXANEDIOL; CYCLOHEXASILOXANE; TRIETHOXYCAPRYLYLSILANE; TOCOPHEROL; CAPRYLYL GLYCOL; DIPROPYLENE GLYCOL; DISTEARDIMONIUM HECTORITE; BUTYLOCTYL SALICYLATE; ETHYLHEXYLGLYCERIN; MAGNESIUM SULFATE; YEAST .BETA.-D-GLUCAN

UV Defense me. Matte Airy-Fit Sunscreen

Active Ingredient

Zinc Oxide 22.24%

Ask Doctor

Children under 6 months of age: Ask a doctor

Do Not Use on damaged or broken skin

Keep out of reach of children. If product is swallowed, get medical help or contact a Poison Control Center right away.

Directions

apply liberally 15 minutes before sun exposure, reapply at least every 12 hours.

Dosage & Administration

Apply 15 minutes before sun exposure, Topical,

warning

For external use only

Do not use on damaged or broken skin

When using this product keep out of eyes

Rinse with water to remove

Inactive ingredients

INCI 50 mL
WATER 15.76491
CYCLOHEXASILOXANE 6
TRIETHOXYCAPRYLYLSILANE 0.38
PROPYLHEPTYL CAPRYLATE 2.49906
TOCOPHEROL 0.01114
BUTYLOCTYL SALICYLATE 2.5
BUTYLENE GLYCOL DICAPRYLATE/DICAPRATE 2.5
DIPROPYLENE GLYCOL 2.5
CAPRYLYL METHICONE 2.5
LAURYL PEG-10 TRIS(...) 1.49985
METHYL METHACRYLATE CROSSPOLYMER 1
DISTEARDIMONIUM HECTORITE 0.4
MAGNESIUM SULFATE 0.4
LAURYL POLYGLYCERYL-3 ... 0.24995
1,2-HEXANEDIOL 0.250001
POLYGLYCERYL-2 TRIISOSTEARATE 0.25
FRAGRANCE 0.1
CAPRYLYL GLYCOL 0.05
ETHYLHEXYLGLYCERIN 0.024975
SODIUM HYALURONATE 0.01
CENTELLA ASIATICA EXTRACT 0.00001
GLYCERIN 0.0000045
BETA-GLUCAN 0.0000005
CAPRYLIC/CAPRIC TRIGLYCERIDE 0.00001
HYDROGENATED LECITHIN 0.0000025
POLYGLYCERYL-10 DIISOSTEARATE 0.000002
MENADIONE 0.0000025

Indications & Usage

Helps prevent sunburn

If used as directed with other sun protection measures, decreases the risk of skin cancer and early skin aging caused by the sun

Purpose

helps prevent sunburn

if used as directed with other sun protection measured, decreases the risk of skin cancer and early skin aging by the sun